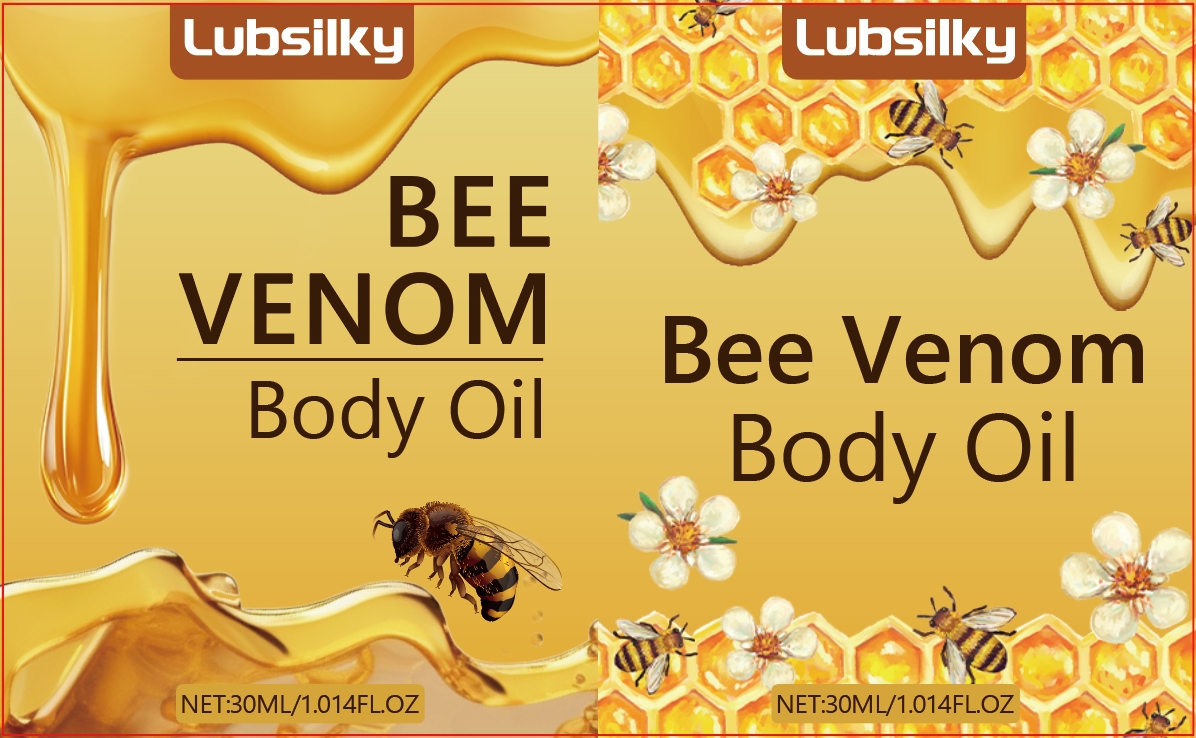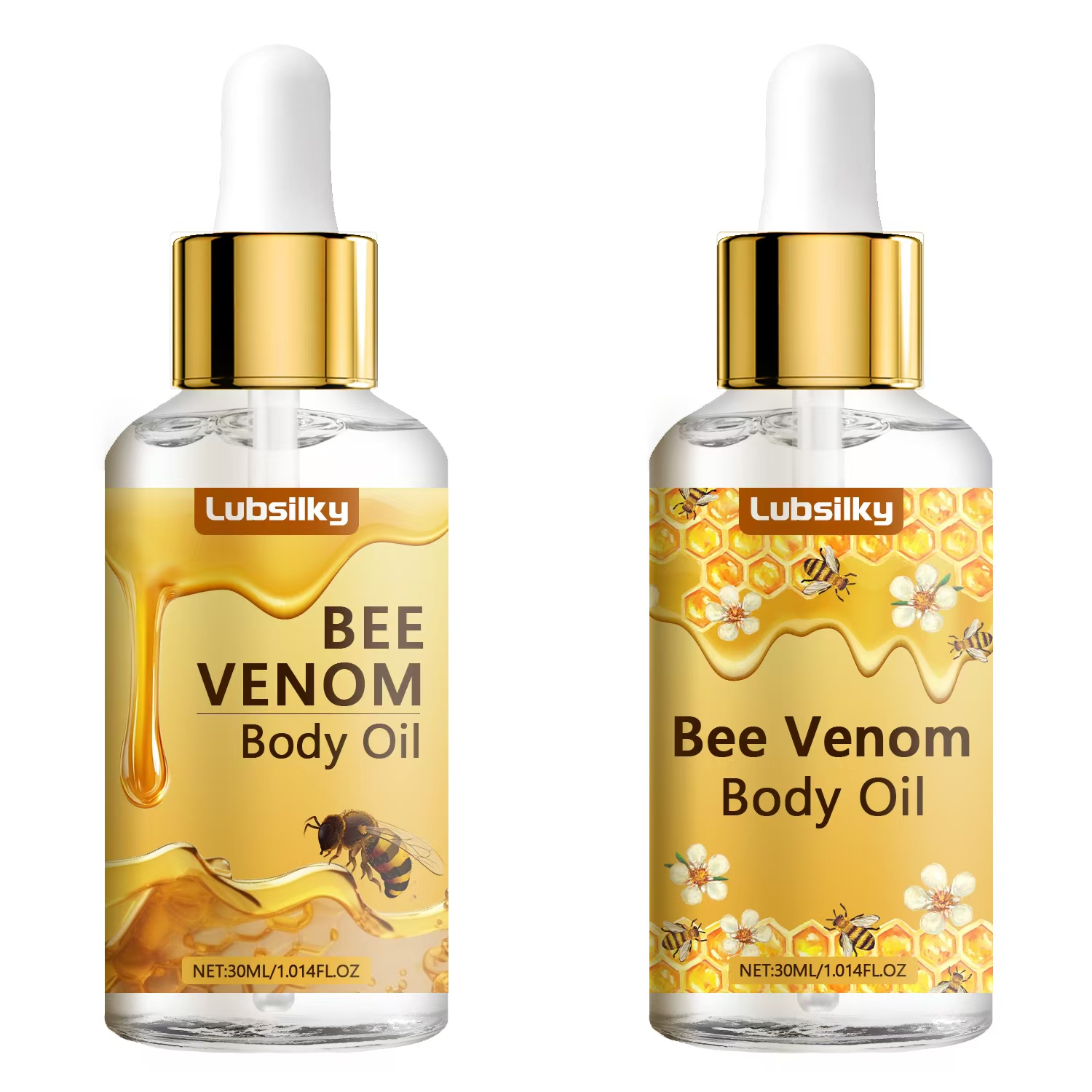 DRUG LABEL: Bee Venom Body Oil
NDC: 84025-236 | Form: OIL
Manufacturer: Guangzhou Yanxi Biotechnology Co., Ltd
Category: otc | Type: HUMAN OTC DRUG LABEL
Date: 20241026

ACTIVE INGREDIENTS: ALOE BARBADENSIS LEAF EXTRACT 5 mg/100 mL; GLYCERIN 3 mg/100 mL
INACTIVE INGREDIENTS: WATER

DOSAGE AND ADMINISTRATION

clean the penis, apply it and gently massage to absorb

WARNINGS

Keep out of children

INACTIVE INGREDIENT

Aqua

INDICATIONS AND USAGE

for body care

Keep out of children

PURPOSE

make the dick thicker, larger, and longer. It can help you to increase feelings of desire and intensify climax.